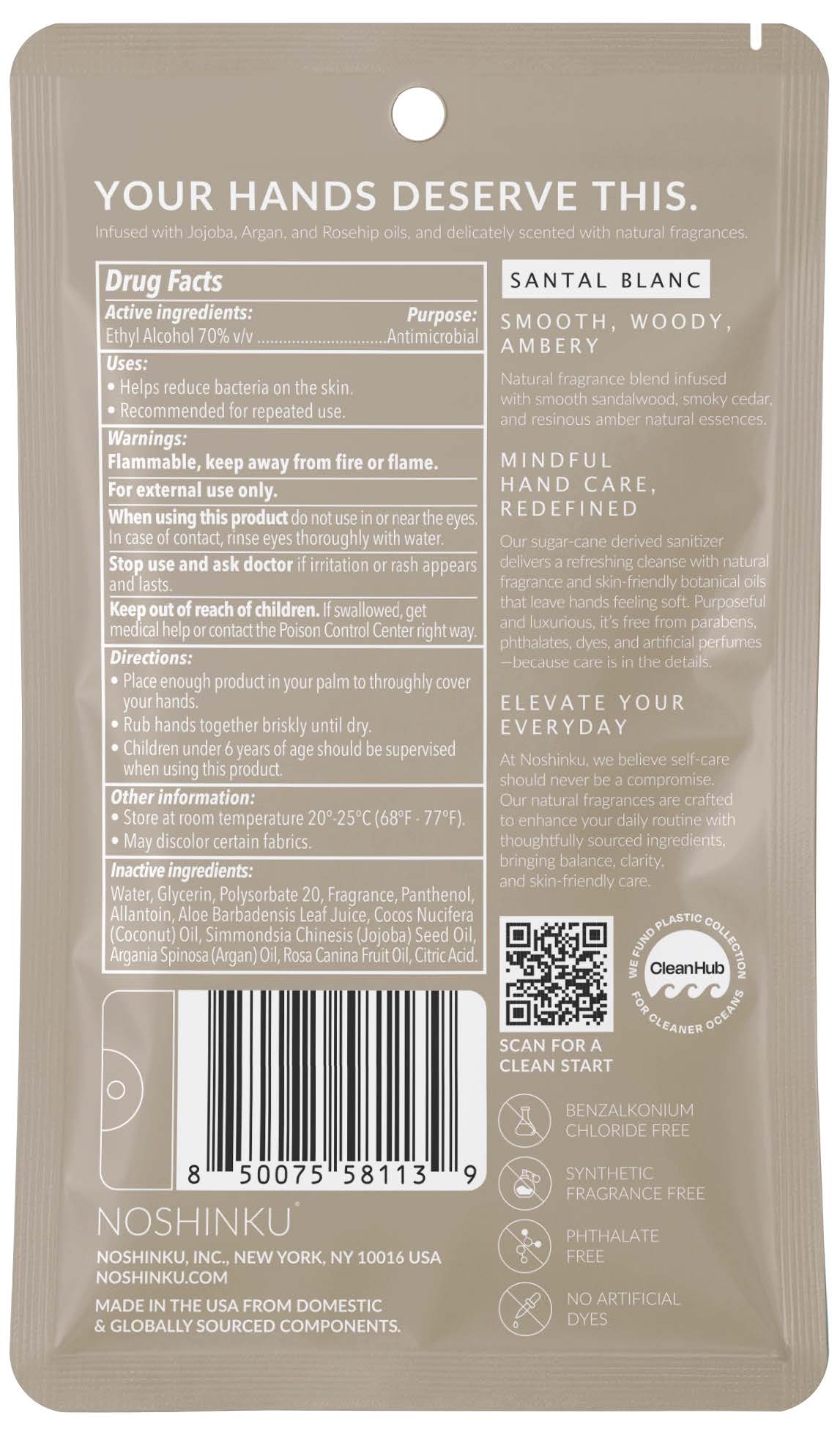 DRUG LABEL: Hand Sanitizer Santal Blanc
NDC: 73898-011 | Form: SOLUTION
Manufacturer: Noshinku
Category: otc | Type: HUMAN OTC DRUG LABEL
Date: 20251222

ACTIVE INGREDIENTS: ALCOHOL 70 mL/100 mL
INACTIVE INGREDIENTS: ALOE BARBADENSIS LEAF POWDER; ROSA CANINA FRUIT OIL; POLYSORBATE 20; SIMMONDSIA CHINENSIS (JOJOBA) SEED OIL; GLYCERIN; ARGANIA SPINOSA KERNEL OIL; CITRIC ACID; WATER; PANTHENOL; ALLANTOIN; COCOS NUCIFERA (COCONUT) OIL

Hand Sanitizer Santal Blanc (73898-011)

Drug Facts

Active Ingredients

Ethyl Alcohol 70% V/V

Purpose

Antimicrobial

Uses

Helps reduce bacteria on the skin.
Recommended for repeated use.

Warnings

Flammable, keep away from fire or flame.
For external use only.

When using this product do not use in or near the eyes. In case of contact, rinse eyes thoroughly with water.

Stop use and consult a doctor if irritation or rash appears and lasts.

Keep out of reach of children. If swallowed, get medical help or contact the Poison Control Center right away.

Directions

Place enough product in your palm to thoroughly cover your hands.
Rub hands together briskly until dry.
Children under 6 years of age should be supervised when using this product.

Other Information

Store at room temperature 20°-25°C (68°F - 77°F)
May discolor certain fabrics

Inactive Ingredients

Water, Glycerin, Polysorbate 20, Fragrance, Panthenol, Allantoin, Aloe Barbadensis Leaf Juice, Cocos Nucifera (Coconut) Oil, Simmondsia Chinesis (Jojoba) Seed Oil, Argania Spinosa (Argan) Oil, Rosa Canina Fruit Oil, Citric Acid.